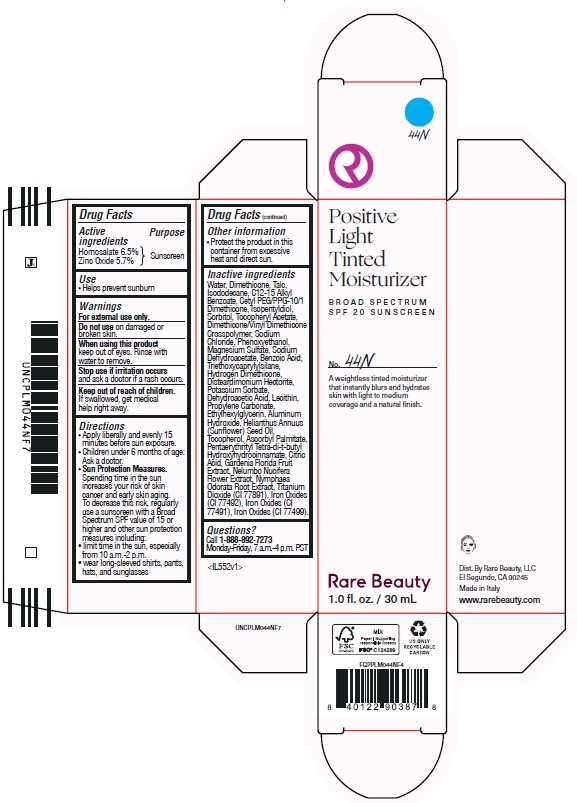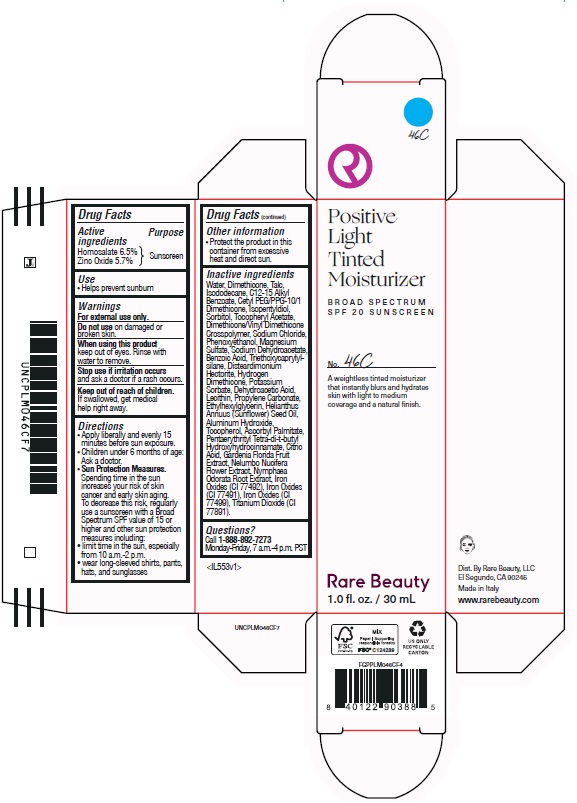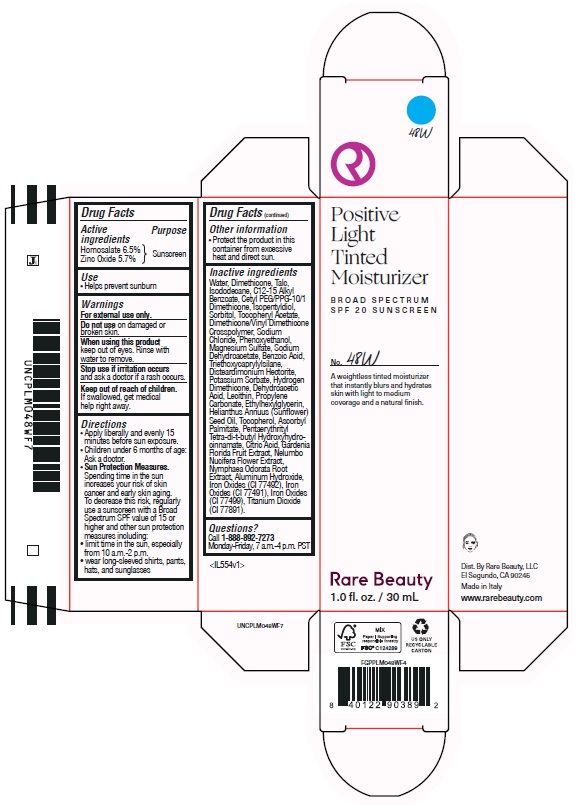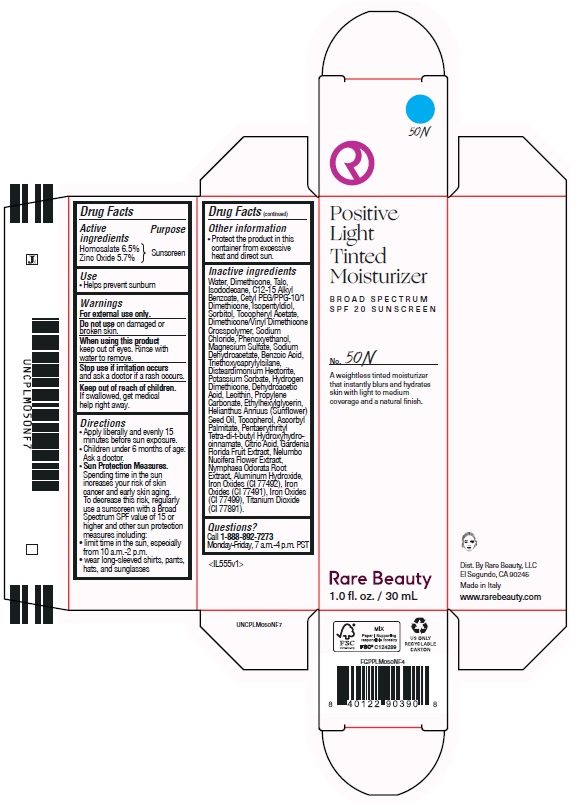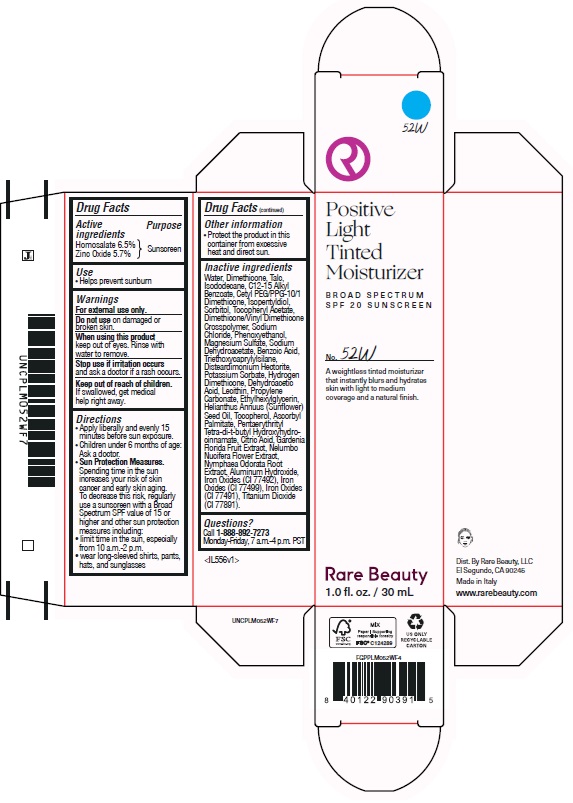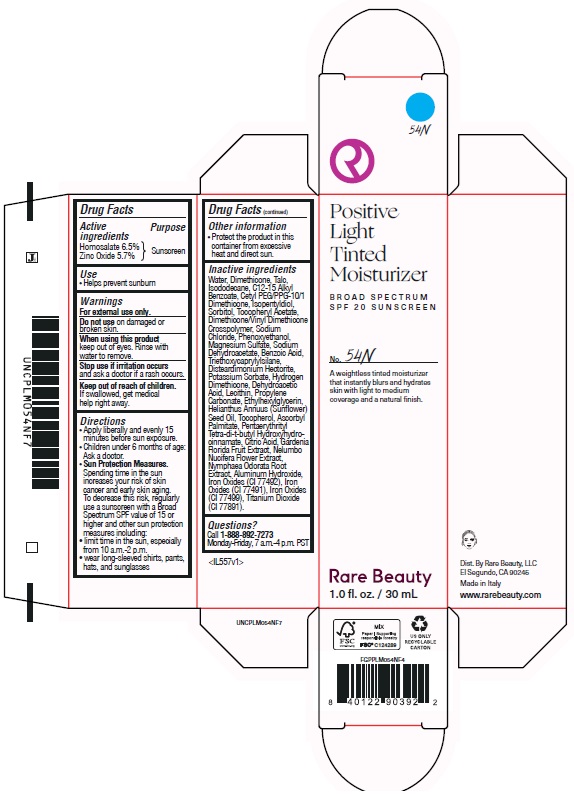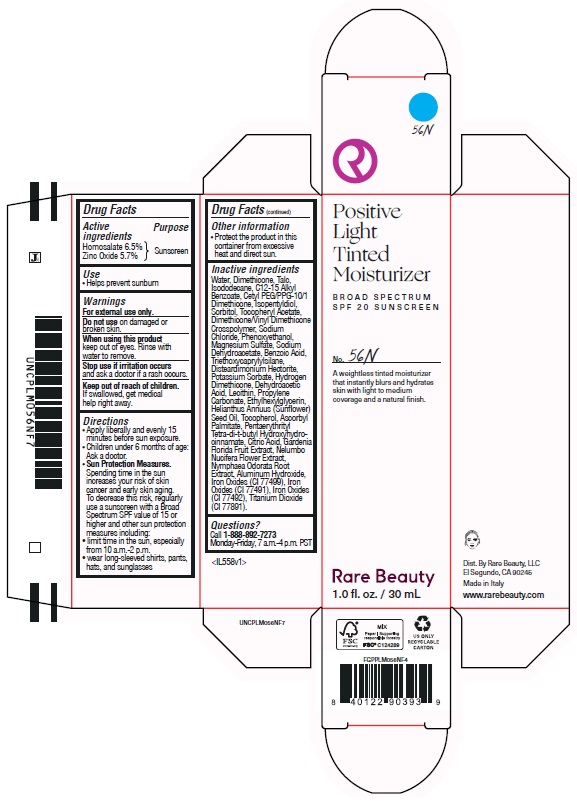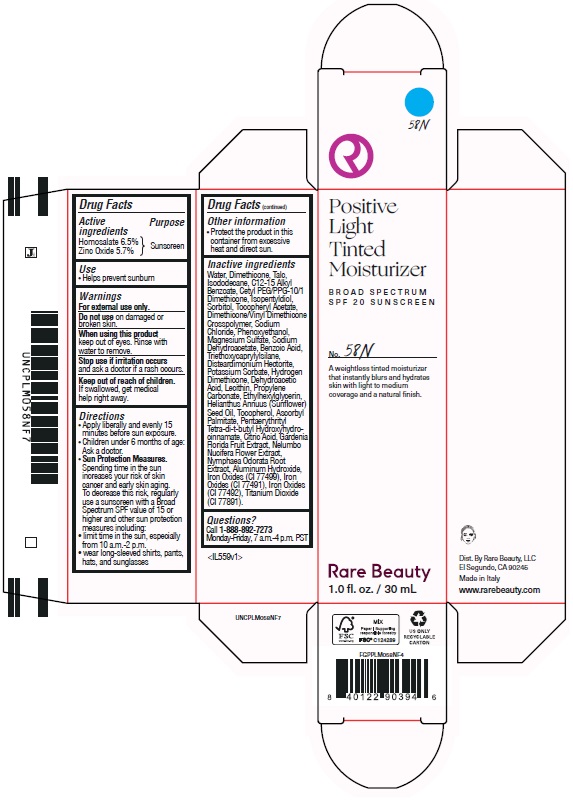 DRUG LABEL: Positive Light Tinted Moisturizer Broad Spectrum SPF 20 Sunscreen 48W
NDC: 82109-142 | Form: LOTION
Manufacturer: Rare Beauty, LLC
Category: otc | Type: HUMAN OTC DRUG LABEL
Date: 20241014

ACTIVE INGREDIENTS: HOMOSALATE 65 mg/1 mL; ZINC OXIDE 57 mg/1 mL
INACTIVE INGREDIENTS: ISOPENTYLDIOL; PHENOXYETHANOL; SODIUM CHLORIDE; HYDROGEN DIMETHICONE (20 CST); POTASSIUM SORBATE; BENZOIC ACID; WATER; DEHYDROACETIC ACID; TOCOPHEROL; ETHYLHEXYLGLYCERIN; ASCORBYL PALMITATE; CITRIC ACID MONOHYDRATE; GARDENIA JASMINOIDES FRUIT; NYMPHAEA ODORATA ROOT; FERRIC OXIDE YELLOW; FERROSOFERRIC OXIDE; TALC; ISODODECANE; CETYL PEG/PPG-10/1 DIMETHICONE (HLB 5); LECITHIN, SOYBEAN; TRIETHOXYCAPRYLYLSILANE; ALKYL (C12-15) BENZOATE; .ALPHA.-TOCOPHEROL ACETATE; DIMETHICONE/VINYL DIMETHICONE CROSSPOLYMER (SOFT PARTICLE); MAGNESIUM SULFATE, UNSPECIFIED; SODIUM DEHYDROACETATE; SUNFLOWER OIL; NELUMBO NUCIFERA FLOWER; FERRIC OXIDE RED; DIMETHICONE; DISTEARDIMONIUM HECTORITE; ALUMINUM HYDROXIDE; PENTAERYTHRITOL TETRAKIS(3-(3,5-DI-TERT-BUTYL-4-HYDROXYPHENYL)PROPIONATE); PROPYLENE CARBONATE; SORBITOL

Positive Light Tinted Moisturizer Broad Spectrum SPF 20 Sunscreen

Active ingredients

Homosalate 6.5%

Zinc Oxide 5.7%

Purpose

Sunscreen

Uses

- Helps prevent sunburn

Warnings

For external use only.

Do not use

on damaged or broken skin.

When using this product

keep out of eyes. Rinse with water to remove.

Stop use if irritation occurs

and ask a doctor if a rash occurs.

Keep out of reach of children.

If swallowed, get medical help right away.

Directions

- Apply liberally and evenly 15 minutes before sun exposure.
- Children under 6 months of age: Ask a doctor.
- Sun Protection Measures. Spending time in the sun increases your risk of skin cancer and early skin aging. To decrease this risk, regularly use a sunscreen with a Broad Spectrum SPF value of 15 or higher and other sun protection measures including
- limit time in the sun, especially from 10 a.m. - 2 p.m.
- wear long-sleeved shirts, pants, hats, and sunglasses

Other Information

Protect the product in this container from excessive heat and direct sun.

Inactive Ingredients

Water, Dimethicone, Talc, Isododecane, C12-15 Alkyl Benzoate, Cetyl PEG/PPG-10/1 Dimethicone, Isopentyldiol, Sorbitol, Tocopheryl Acetate, Dimethicone/Vinyl Dimethicone Crosspolymer, Sodium Chloride, Phenoxyethanol, Magnesium Sulfate, Sodium Dehydroacetate, Benzoic Acid, Hydrogen Dimethicone, Triethoxycaprylylsilane, Disteardimonium Hectorite, Potassium Sorbate, Aluminum Hydroxide, Dehydroacetic Acid, Lecithin, Propylene Carbonate, Ethylhexylglycerin, Helianthus Annuus (Sunflower) Seed Oil, Tocopherol, Ascorbyl Palmitate, Pentaerythrityl Tetra-di-t-butyl Hydroxyhydrocinnamate, Citric Acid, Gardenia Florida Fruit Extract, Nelumbo Nucifera Flower Extract, Nymphaea Odorata Root Extract, Titanium Dioxide (CI 77891), Iron Oxides (CI 77492), Iron Oxides (CI 77491), Iron Oxides (CI 77499).

Questions?

Call 1-888-892-7273

Monday-Friday, 7am-4pm PST

Company Information

Dist. By Rare Beauty, LLC

El Segundo, CA 90245

Made in Italy

www.rarebeauty.com